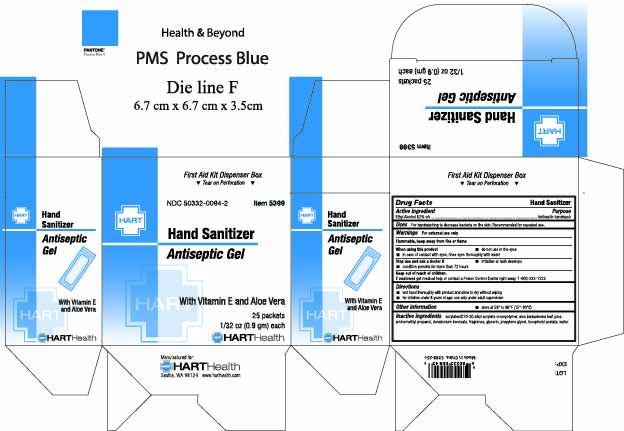 DRUG LABEL: Hand Sanitizer
NDC: 50332-0094 | Form: GEL
Manufacturer: HART Health
Category: otc | Type: HUMAN OTC DRUG LABEL
Date: 20251202

ACTIVE INGREDIENTS: ALCOHOL 62 g/100 g
INACTIVE INGREDIENTS: ACRYLATES/C10-30 ALKYL ACRYLATE CROSSPOLYMER (60000 MPA.S); ALOE BARBADENSIS LEAF JUICE; AMINOMETHYL PROPANOL; DENATONIUM BENZOATE; GLYCERIN; PROPYLENE GLYCOL; WATER

Hand Sanitizer Antiseptic Gel

Active Ingredients

Ethyl Alcohol 62% v/v

Purpose

Antiseptic handwash

Uses

For hanwashing to help decrease bacteria on the skin. Recommended for repeated use.

Warnings

For external use only

Flammable, keep away from heat and flame

When using this product

- do not use in the eyes
- in case of contact, rinse eyes throughly with water

Stop use and ask a doctor if

- irritation and redness develop
- condition persists for more than 72 hours

Keep out of reach of children

If swallowed, get medical help or contact a Poison Control Center right away. 1-800-222-1222

Directions

- wet hands thoroughly with product and allow to dry without wiping
- for children under 6 years of age; use only under adult supervision

OTHER SAFETY INFORMATION

- Store at 59° to 86°F (15-30°C)

Inactive ingrediends

acrylates/C10-30 alkyl acrylate crosspolymer, aloe barbadensis leaf juice, aminomethyl propanol, denatonium benzoate, fragrance, glycerin, propylene glycol, tocopheryl acetate, water.